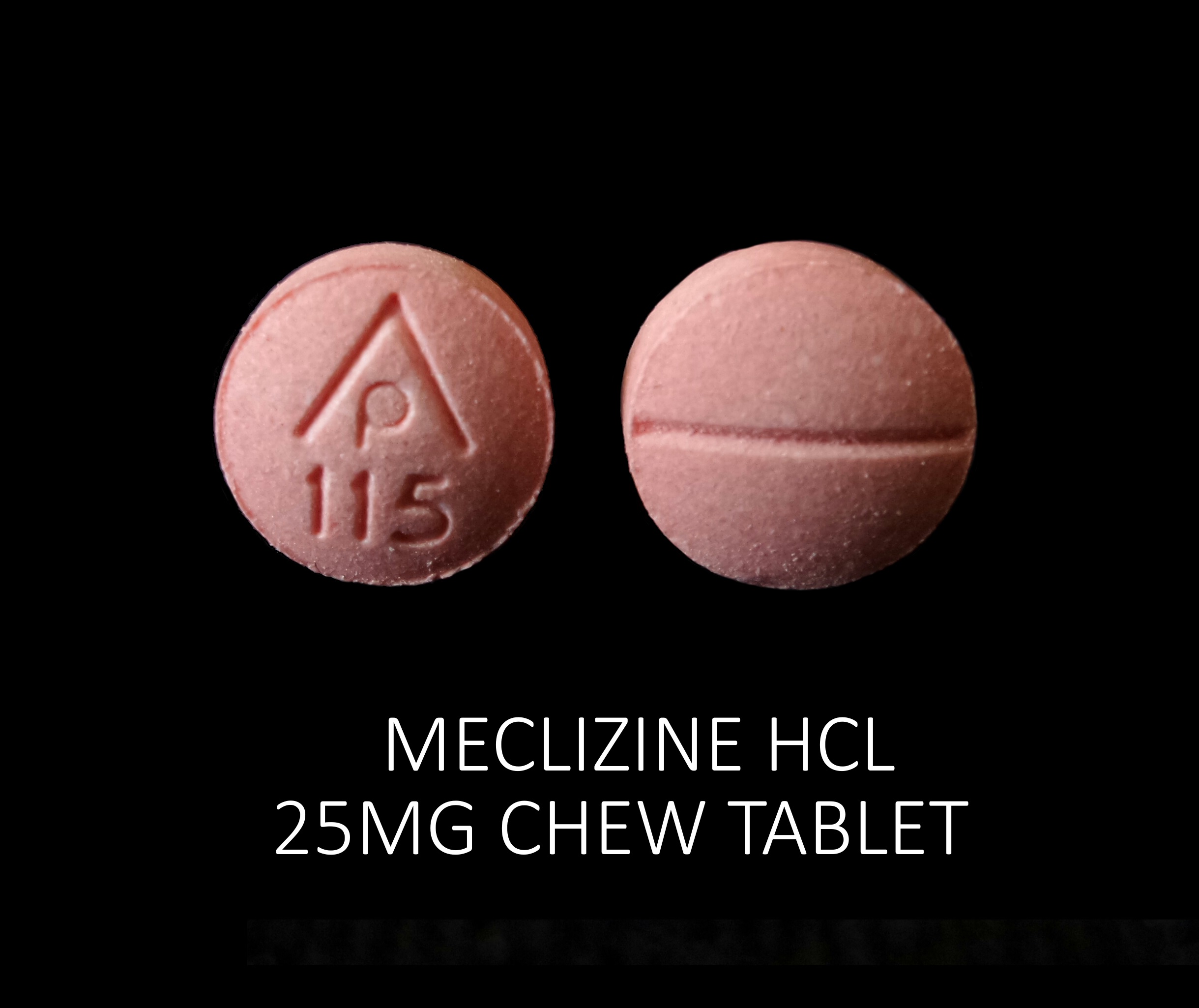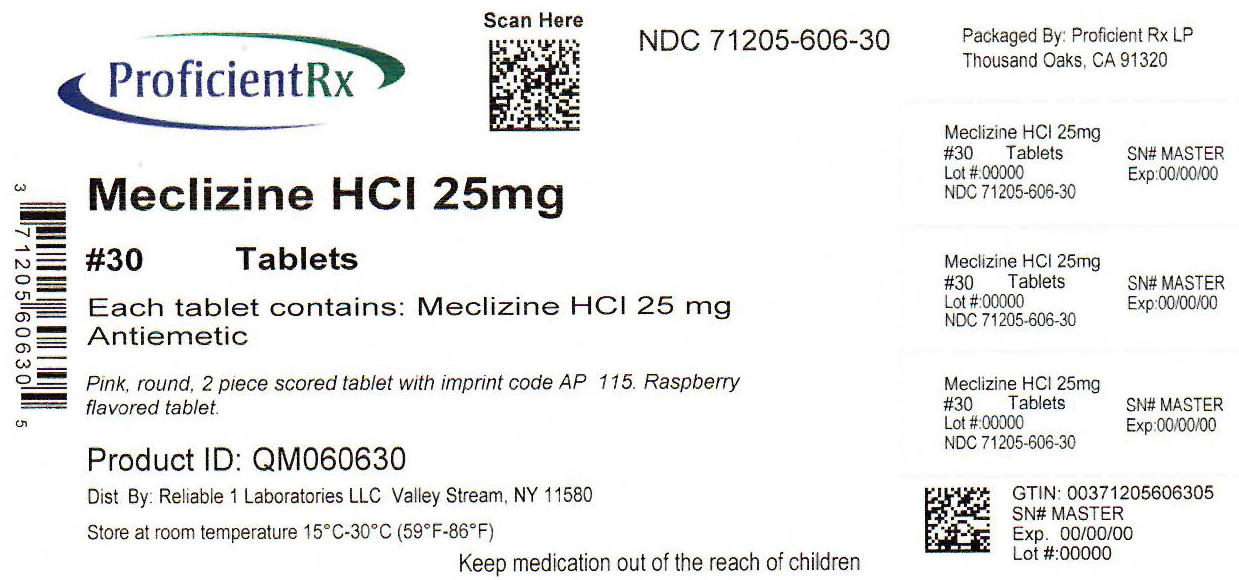 DRUG LABEL: Meclizine HCL 25 mg
NDC: 71205-606 | Form: TABLET
Manufacturer: Proficient Rx LP
Category: otc | Type: HUMAN OTC DRUG LABEL
Date: 20251001

ACTIVE INGREDIENTS: MECLIZINE HYDROCHLORIDE 25 mg/1 1
INACTIVE INGREDIENTS: DEXTROSE, UNSPECIFIED FORM; FD&C RED NO. 40; MAGNESIUM STEARATE; MICROCRYSTALLINE CELLULOSE; RASPBERRY; ASPARTAME; SUCROSE; CROSCARMELLOSE SODIUM

Meclizine HCL 25 mg

Active ingredient (in each tablet)

Meclizine HCL 25 mg

Purpose

Antiemetic

Uses

- prevents and treats nausea, vomiting or dizziness due to motion sickness
- for others uses, consult your doctor

Warnings

Ask a doctor before use if you have

- glaucoma
- a breathing problem such as emphysema or chronic bronchitis
- trouble urinating due to an enlarged prostate gland

Ask a doctor or pharmacist before use if you are taking sedatives or tranquilizers

When using this prodcut

- you may get drowsy
- avoid alcoholic drinks
- alcohol, sedatives and tranquilizers may increase drowsiness
- be careful when driving a motor vehicle or operating machinery

If pregnant or breast-feeding, ask a health professional before use.

Keep out of reach of children. In case of overdose, get medical help or contact a Poison Control Center right away.

Ask a doctor before use if you have

- glaucoma
- a breathing problem such as emphysema or chronic bronchitis
- trouble urinating due to an enlarged prostate gland

Ask a doctor or pharmacist before use if you are taking sedatives or tranquilizers

When using this product

- you may get drowsy
- avoid alcoholic drinks
- alcohol, sedatives and tranquilizers may increase drowsiness
- be careful when driving a motor vehicle or operating machinery

PREGNANCY OR BREAST FEEDING

If pregnant or breast-feeding, ask a health professional before use.

Keep out of reach of children. In case of overdose, get medical help or contact a Poison Control Center right away.

Directions

- take dose one hour before travel starts
- tablets can be chewed or swallowed whole with water

adults & children 12 years and over: 1-2 tablets once daily

children unser 12 years: ask a doctor

Other information

- Phenylketonurics: each tablet contrains: phenylalanine 0.28 mg
- store at room temperature 15°-30°C (59°-86°F)
- This is a bulf package. Dispense contents with a child-resistant closure in a tight, light-resistant container as defined in the USP.

Inactive ingredients

aspartame, compressible sugar, croscarmellose sodium, dextrose, FD&C red # 40 (Al-lake), magnesium stearate, microcrystalline cellulose, raspberry flavor

Questions or comments?

call 516-341-0666, 8:30 am - 4:30 pm ET, Monday - Friday

TAMPER EVIDENT: DO NOT USE IF IMPRINTED SAFETY SEAL UNDER CAP IS BROKEN OR MISSING

*Reliable 1 Laboratories LLC is not affiliated with the owner of the trademark BONINE®.

Distributed by: Reliable 1 Laboratories LLC, Valley Stream, NY 11580

Repackaged by: Proficient Rx LP Thousand Oaks, CA 91320

www.reliable1labs.com

PACKAGE LABEL

NDC 71205-606-30

Meclizine HCL 25 mg

ANTIEMETIC

30 TABLETS

THIS PACKAGE FOR HOUSEHOLD WITHOUT YOUNG CHILDREN

*Compare to Active Ingredient in BONINE®